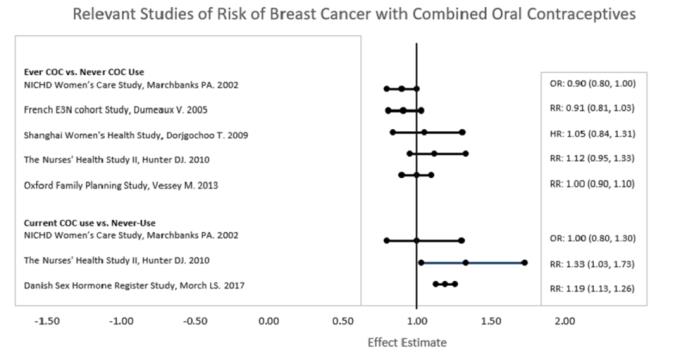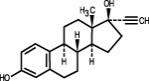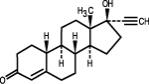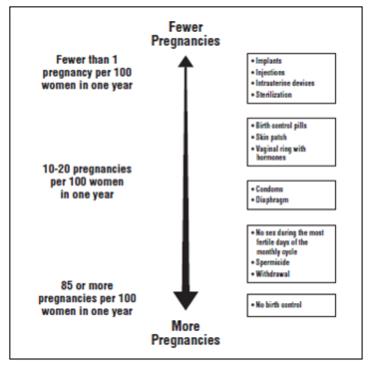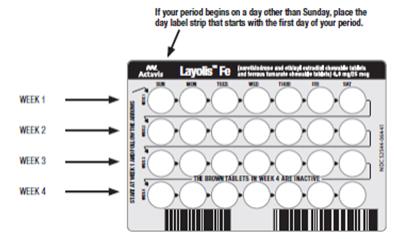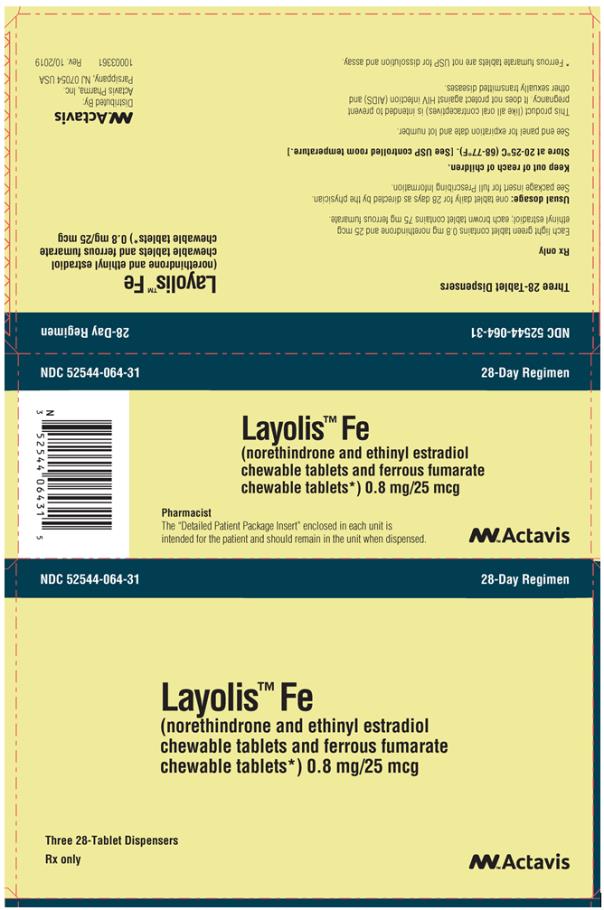 DRUG LABEL: Layolis Fe
NDC: 52544-064 | Form: KIT | Route: ORAL
Manufacturer: Actavis Pharma, Inc.
Category: prescription | Type: HUMAN PRESCRIPTION DRUG LABEL
Date: 20240322

ACTIVE INGREDIENTS: NORETHINDRONE 0.8 mg/1 1; ETHINYL ESTRADIOL 0.025 mg/1 1
INACTIVE INGREDIENTS: D&C YELLOW NO. 10; FD&C BLUE NO. 1; FD&C YELLOW NO. 6; LACTOSE MONOHYDRATE; MAGNESIUM STEARATE; MANNITOL; CELLULOSE, MICROCRYSTALLINE; POVIDONE; SODIUM STARCH GLYCOLATE TYPE A POTATO; SPEARMINT; SUCRALOSE; ALPHA-TOCOPHEROL; FERROUS FUMARATE 75 mg/1 1; MAGNESIUM STEARATE; MANNITOL; CELLULOSE, MICROCRYSTALLINE; POVIDONE; SODIUM STARCH GLYCOLATE TYPE A POTATO; SPEARMINT; SUCRALOSE

HIGHLIGHTS OF PRESCRIBING INFORMATION

These highlights do not include all the information needed to use LAYOLIS Fe safely and effectively. See full prescribing information for LAYOLIS Fe.
LAYOLIS® Fe (norethindrone and ethinyl estradiol chewable tablets and ferrous fumarate chewable tablets)
Initial U.S. Approval: 1974

WARNING: CIGARETTE SMOKING AND SERIOUS CARDIOVASCULAR EVENTS

See full prescribing information for complete boxed warning.

- Women over 35 years old who smoke should not use LAYOLIS Fe. (4)
- Cigarette smoking increases the risk of serious cardiovascular events from combination oral contraceptive (COC) use. (4)

1 INDICATIONS AND USAGE

- LAYOLIS Fe is a combination of norethindrone, a progestin, and ethinyl estradiol, an estrogen, indicated for use by females of reproductive potential to prevent pregnancy. (1)
- The efficacy in females of reproductive potential with a body mass index (BMI) of > 35 kg/m^2 has not been evaluated. (1, 8.8)

2 DOSAGE AND ADMINISTRATION

- Chew one tablet without water at the same time every day. (2.1)
- Take tablets in the order directed on the blister pack. (2.1)

3 DOSAGE FORMS AND STRENGTHS

LAYOLIS Fe consists of 28 tablets in the following order (3):

- 24 light green, round tablets (active) each containing 0.8 mg norethindrone and 0.025 mg ethinyl estradiol.
- 4 brown, round tablets (non-hormonal placebo) each containing 75 mg ferrous fumarate, which does not serve any therapeutic purpose.

4 CONTRAINDICATIONS

- A high risk of arterial or venous thrombotic diseases. (4)
- Undiagnosed abnormal uterine bleeding. (4)
- Breast cancer (4)
- Liver tumors or liver disease (4)
- Co-administration with Hepatitis C drug combinations containing ombitasvir/paritaprevir/ritonavir, with or without dasabuvir. (4)

5 WARNINGS AND PRECAUTIONS

- Vascular risks: Stop LAYOLIS Fe if a thrombotic event occurs. Stop at least 4 weeks before and through 2 weeks after major surgery. Start no earlier than 4 weeks after delivery in women who are not breastfeeding. (5.1)
- Liver disease: Discontinue if jaundice occurs. (5.3)
- High blood pressure: Do not prescribe for women with uncontrolled hypertension or hypertension with vascular disease. (5.5)
- Carbohydrate and lipid metabolic effects: Monitor prediabetic and diabetic women taking LAYOLIS Fe. Consider an alternate contraceptive method for women with uncontrolled dyslipidemia. (5.7)
- Headache: Evaluate significant change in headaches and discontinue if indicated. (5.8).
- Uterine bleeding: Evaluate irregular bleeding or amenorrhea. (5.9)

6 ADVERSE REACTIONS

The most common adverse reactions (≥ 2%) are nausea/vomiting (8.8%), headaches/migraine (7.5%), depression/mood complaints (4.1%), dysmenorrhea (3.9%), acne (3.2%), anxiety symptoms (2.4%), breast pain/tenderness (2.4%), and increased weight (2.3%). (6.1)

To report SUSPECTED ADVERSE REACTIONS, contact Actavis at 1-888-838-2872 or FDA at 1-800-FDA-1088 or www.fda.gov/medwatch.

7 DRUG INTERACTIONS

- Drugs or herbal products that induce certain enzymes, including CYP3A4, may decrease the effectiveness of COCs or increase breakthrough bleeding. Counsel patients to use a back-up method or alternative method of contraception when enzyme inducers are used with COCs. (7.1)

8 USE IN SPECIFIC POPULATIONS

- Lactation: Not recommended, LAYOLIS Fe can decrease milk production. (8.2)

FULL PRESCRIBING INFORMATION

WARNING: CIGARETTE SMOKING AND SERIOUS CARDIOVASCULAR EVENTS

Cigarette smoking increases the risk of serious cardiovascular events from combination oral contraceptive (COC) use. This risk increases with age, particularly in women over 35 years of age, and with the number of cigarettes smoked. For this reason, COCs should not be used by women who are over 35 years of age and smoke [see Contraindications (4) and Warnings and Precautions (5.1)].

1 INDICATIONS AND USAGE

LAYOLIS Fe is indicated for use by women to prevent pregnancy.

The efficacy of LAYOLIS Fe in women with a body mass index (BMI) of > 35 kg/m^2 has not been evaluated.

2 DOSAGE AND ADMINISTRATION

2.1 How to Take LAYOLIS Fe

To achieve maximum contraceptive effectiveness, LAYOLIS Fe must be taken exactly as directed. Chew and swallow one tablet without water at the same time every day. Tablets must be taken in the order directed on the blister pack. Tablets should not be skipped or taken at intervals exceeding 24 hours. LAYOLIS Fe may be administered without regard to meals [see Clinical Pharmacology (12.3)].

2.2 How to Start LAYOLIS Fe

Instruct the patient to begin taking LAYOLIS Fe on Day 1 of her menstrual cycle (that is, the first day of her menstrual bleeding). One light green tablet should be taken daily for 24 consecutive days followed by one brown tablet daily for 4 consecutive days. Instruct the patient to use a non-hormonal contraceptive as back-up during the first 7 days if she starts taking LAYOLIS Fe other than on the first day of her menstrual cycle.

For postpartum women who do not breastfeed or after a second trimester abortion, LAYOLIS Fe may be started no earlier than 4 weeks postpartum. Recommend use of a non-hormonal back-up method for the first 7 days. When combined oral contraceptives (COCs) are used during the postpartum period, the increased risk of thromboembolic disease associated with the postpartum period must be considered. The possibility of ovulation and conception before starting COCs should also be considered.

If the patient is switching from a combination hormonal method such as:
- Another pill
- Vaginal ring
- Patch

- Instruct her to take the first light green pill on the day she would have started a new cycle of her previous birth control pack (Day 1).
- If she previously used a vaginal ring or transdermal patch, she should start using LAYOLIS Fe on the day she would have restarted the ring or patch.
- Instruct the patient to use a non-hormonal back-up method such as a condom and spermicide for the first 7 days.

If the patient is switching from a progestin-only method such as:
- Progestin-only pill
- Implant
- Intrauterine system
- Injection

- Instruct her to take the first light green pill on the day she would have taken her next progestin-only pill or on the day of removal of her implant or intrauterine system or on the day when she would have had her next injection.
- Instruct the patient to use a non-hormonal back-up method such as a condom and spermicide for the first 7 days.

2.3 Missed Doses

Table 1. Instructions for Missed LAYOLIS Fe Tablets
If one light green tablet is missed | Take the missed tablet as soon as possible. Take the next tablet at the regular time. Continue taking one tablet a day until the pack is finished. Additional nonhormonal contraception (such as condoms) is not needed.
If two light green tablets in a row are missed in Week 1 or Week 2 of the tablet pack | Take the two missed tablets as soon as possible, and the next two tablets the next day. Continue taking one tablet a day until the pack is finished. Use additional nonhormonal contraception (such as condoms) until hormonal tablets have been taken for 7 days after missing tablets.
If two light green tablets in a row are missed in Week 3 or Week 4 of the tablet pack | Throw away the remainder of the tablet pack. Start a new tablet pack the same day. Use additional nonhormonal contraception (such as condoms) until hormonal tablets have been taken for 7 days after missing tablets.
If three or more light green tablets in a row are missed | Throw away the missed tablets. Continue taking one tablet every day as indicated on the pack until the pack is finished. Bleeding may occur during the week following the missed tablets. Use additional nonhormonal contraception (such as condoms) until hormonal tablets have been taken for 7 days after missing tablets.
If any of the four brown tablets are missed | Throw away the missed tablets. Continue taking the remaining tablets until the pack is finished. Additional nonhormonal contraception (such as condoms) is not needed.

2.4 Advice in Case of Gastrointestinal Disturbances

In case of severe vomiting or diarrhea, absorption may not be complete and additional contraceptive measures should be taken. If vomiting or diarrhea occurs within 3-4 hours after taking a light green tablet, this can be regarded as a missed tablet [see Dosage and Administration (2.3)].

3 DOSAGE FORMS AND STRENGTHS

LAYOLIS Fe is available in blister packs.

Each blister pack (28 tablets) contains in the following order:

- 24 light green, round tablets (active) imprinted with “WC” on one side and “483” on the other and each containing 0.8 mg norethindrone and 0.025 mg ethinyl estradiol.
- 4 brown, round tablets (non-hormonal placebo) imprinted with “WC” on one side and “624” on the other and each containing 75 mg ferrous fumarate. The ferrous fumarate chewable tablets do not serve any therapeutic purpose.

4 CONTRAINDICATIONS

LAYOLIS FE is contraindicated in females who are known to have or develop the following conditions:

- A high risk of arterial or venous thrombotic diseases. Examples include women who are known to:
  - Smoke, if over age 35 [see Boxed Warning, and Warnings and Precautions (5.1)]
  - Have deep vein thrombosis or pulmonary embolism, now or in the past [see Warnings and Precautions (5.1)]
  - Have cerebrovascular disease [see Warnings and Precautions (5.1)]
  - Have coronary artery disease [see Warnings and Precautions (5.1)]
  - Have thrombogenic valvular or thrombogenic rhythm diseases of the heart (for example, subacute bacterial endocarditis with valvular disease, or atrial fibrillation) [see Warnings and Precautions (5.1)]
  - Have inherited or acquired hypercoagulopathies [see Warnings and Precautions (5.1)]
  - Have uncontrolled hypertension [see Warnings and Precautions (5.5)]
  - Have diabetes with vascular disease [see Warnings and Precautions (5.7)]
  - Have headaches with focal neurological symptoms or have migraine headaches with or without aura if over age 35 [see Warnings and Precautions (5.8)]
- Current diagnosis of, or history of, breast cancer, which may be hormone-sensitive [see Warnings and Precautions (5.2)]
- Liver tumors, benign or malignant, or liver disease [see Warnings and Precautions (5.3), Use in Specific Populations (8.7), and Clinical Pharmacology (12.3)]
- Undiagnosed abnormal uterine bleeding [see Warnings and Precautions (5.9)]
- Use of Hepatitis C drug combinations containing ombitasvir/paritaprevir/ritonavir, with or without dasabuvir, due to the potential for ALT elevations [see Warnings and Precautions (5.4)]

5 WARNINGS AND PRECAUTIONS

5.1 Thrombotic and Other Vascular Events

Stop LAYOLIS Fe if an arterial or deep venous thrombotic (VTE) event occurs. Although the use of COCs increases the risk of venous thromboembolism, pregnancy increases the risk of venous thromboembolism as much or more than the use of COCs. The risk of venous thromboembolism in women using COCs is 3 to 9 per 10,000 woman-years. The excess risk is highest during the first year of use of a COC. Use of COCs also increases the risk of arterial thromboses such as strokes and myocardial infarctions, especially in women with other risk factors for these events. The risk of thromboembolic disease due to oral contraceptives gradually disappears after COC use is discontinued.

If feasible, stop LAYOLIS Fe at least 4 weeks before and through 2 weeks after major surgery or other surgeries known to have an elevated risk of thromboembolism.

Start LAYOLIS Fe no earlier than 4 weeks after delivery, in women who are not breastfeeding. The risk of postpartum thromboembolism decreases after the third postpartum week, whereas the risk of ovulation increases after the third postpartum week.

COCs have been shown to increase both the relative and attributable risks of cerebrovascular events (thrombotic and hemorrhagic strokes), although, in general, the risk is greatest among older (> 35 years of age), hypertensive women who also smoke. COCs also increase the risk for stroke in women with other underlying risk factors.

Oral contraceptives must be used with caution in women with cardiovascular disease risk factors.

Stop LAYOLIS Fe if there is unexplained loss of vision, proptosis, diplopia, papilledema, or retinal vascular lesions. Evaluate for retinal vein thrombosis immediately.

5.2 Malignant Neoplasms

Breast Cancer

LAYOLIS Fe is contraindicated in females who currently have or have had breast cancer because breast cancer may be hormonally sensitive [see Contraindications (4)].

Epidemiology studies have not found a consistent association between use of combined oral contraceptives (COCs) and breast cancer risk. Studies do not show an association between ever (current or past) use of COCs and risk of breast cancer. However, some studies report a small increase in the risk of breast cancer among current or recent users (<6 months since last use) and current users with longer duration of COC use [see Adverse Reactions (6.2)].

Cervical Cancer

Some studies suggest that COCs are associated with an increase in the risk of cervical cancer or intraepithelial neoplasia. However, there is controversy about the extent to which these findings may be due to differences in sexual behavior and other factors.

5.3 Liver Disease

Discontinue LAYOLIS Fe if jaundice develops. Steroid hormones may be poorly metabolized in patients with impaired liver function. Acute or chronic disturbances of liver function may necessitate the discontinuation of COC use until markers of liver function return to normal and COC causation has been excluded.

Hepatic adenomas are associated with COC use. An estimate of the attributable risk is 3.3 cases/100,000 COC users. Rupture of hepatic adenomas may cause death through intra-abdominal hemorrhage.

Studies have shown an increased risk of developing hepatocellular carcinoma in long-term (> 8 years) COC users. However, the attributable risk of liver cancers in COC users is less than one case per million users.

Oral contraceptive-related cholestasis may occur in women with a history of pregnancy-related cholestasis. Women with a history of COC-related cholestasis may have the condition recur with subsequent COC use.

5.4 Risk of Liver Enzyme Elevations with Concomitant Hepatitis C Treatment

During clinical trials with Hepatitis C combination drug regimen that contains ombitasvir/paritaprevir/ritonavir, with or without dasabuvir, ALT elevations greater than 5 times the upper limit of normal (ULN), including some cases greater than 20 times the ULN, were significantly more frequent in women using ethinyl estradiol-containing medications, such as COCs. Discontinue LAYOLIS Fe prior to starting therapy with the combination drug regimen ombitasvir/paritaprevir/ritonavir, with or without dasabuvir [see Contraindications (4)]. LAYOLIS Fe can be restarted approximately 2 weeks following completion of treatment with the Hepatitis C combination drug regimen.

5.5 High Blood Pressure

For women with well-controlled hypertension, monitor blood pressure and stop LAYOLIS Fe if blood pressure rises significantly. Women with uncontrolled hypertension or hypertension with vascular disease should not use COCs.

An increase in blood pressure has been reported in women taking COCs, and this increase is more likely in older women and with extended duration of use. The incidence of hypertension increases with increasing concentration of progestin.

5.6 Gallbladder Disease

Studies suggest the relative risk of developing gallbladder disease may be increased among COC users.

5.7 Carbohydrate and Lipid Metabolic Effects

Carefully monitor prediabetic and diabetic women who are taking LAYOLIS Fe. COCs may decrease glucose tolerance in a dose-related fashion.

Consider alternative contraception for women with uncontrolled dyslipidemia. A small proportion of women will have adverse lipid changes while on COCs.

Women with hypertriglyceridemia, or a family history thereof, may be at an increased risk of pancreatitis when using COCs.

5.8 Headache

If a woman taking LAYOLIS Fe develops new headaches that are recurrent, persistent, or severe, evaluate the cause and discontinue LAYOLIS Fe if indicated.

An increase in frequency or severity of migraine during COC use (which may be prodromal of a cerebrovascular event) may be a reason for immediate discontinuation of the COC.

5.9 Bleeding Irregularities

Unscheduled (breakthrough or intracyclic) bleeding and spotting sometimes occur in patients on COCs, especially during the first three months of use. If bleeding persists or occurs after previously regular cycles, check for causes such as pregnancy or malignancy. If pathology and pregnancy are excluded, bleeding irregularities may resolve over time or with a change to a different COC.

Patient diaries from the clinical trial of LAYOLIS Fe showed that on the first cycle of use, 37% of subjects taking LAYOLIS Fe had unscheduled bleeding and/or spotting. From Cycle 2-13, the percent of women with unscheduled bleeding/spotting ranged from 21-31% per cycle. For those women with unscheduled bleeding/spotting, the mean number of days of unscheduled bleeding/spotting was 5.2 in the first cycle of use and ranged from 3.6 – 4.2 in cycles 2-13. A total of 15 subjects out of 1,677 (0.9%) discontinued the study prematurely due to metrorrhagia or irregular menstruation.

Women who are not pregnant and use LAYOLIS Fe may not have scheduled (withdrawal) bleeding every cycle or may experience amenorrhea (absence of any bleeding and spotting). The incidence of amenorrhea in the clinical trial increased from 8.1% of the subjects in Cycle 2 to 18.4% by Cycle 13. For those women who had scheduled (withdrawal) bleeding, the average duration of bleeding per cycle in Cycles 2-13 was 3.7 days.

If the patient has not adhered to the prescribed dosing schedule (missed one or more active tablets or started taking them on a day later than she should have), consider the possibility of pregnancy at the time of the first missed period and take appropriate diagnostic measures. If the patient has adhered to the prescribed regimen and misses two consecutive periods, rule out pregnancy.

Some women may encounter amenorrhea or oligomenorrhea after stopping COCs, especially when such a condition was pre-existent.

5.10 COC Use Before or During Early Pregnancy

Extensive epidemiological studies have revealed no increased risk of birth defects in women who have used oral contraceptives prior to pregnancy. Studies also do not suggest a teratogenic effect, particularly in so far as cardiac anomalies and limb-reduction defects are concerned, when taken inadvertently during early pregnancy. LAYOLIS Fe use should be discontinued if pregnancy is confirmed.

The administration of oral contraceptives to induce withdrawal bleeding should not be used as a test for pregnancy [see Use in Specific Populations (8.1)].

5.11 Depression

Women with a history of depression should be carefully observed and LAYOLIS Fe discontinued if depression recurs to a serious degree.

5.12 Interference with Laboratory Tests

The use of COCs may change the results of some laboratory tests, such as coagulation factors, lipids, glucose tolerance, and binding proteins. Women on thyroid hormone replacement therapy may need increased doses of thyroid hormone because serum concentrations of thyroid-binding globulin increase with use of COCs.

5.13 Monitoring

A woman who is taking COCs should have a yearly visit with her healthcare provider for a blood pressure check and for other indicated healthcare.

5.14 Other Conditions

In women with hereditary angioedema, exogenous estrogens may induce or exacerbate symptoms of angioedema. Chloasma may occasionally occur, especially in women with a history of chloasma gravidarum. Women with a tendency to chloasma should avoid exposure to the sun or ultraviolet radiation while taking COCs.

6 ADVERSE REACTIONS

The following serious adverse reactions with the use of COCs are discussed elsewhere in the labeling:

- Serious cardiovascular events and smoking [see Boxed Warning, and Warnings and Precautions (5.1)]
- Vascular events [see Warnings and Precautions (5.1)]
- Liver disease [see Warnings and Precautions (5.3)]

Adverse reactions commonly reported by COC users are:

- Irregular uterine bleeding
- Nausea
- Breast tenderness
- Headache

6.1 Clinical Trial Experience

Because clinical trials are conducted under widely varying conditions, adverse reaction rates observed in the clinical trials of a drug cannot be directly compared to rates in the clinical trials of another drug and may not reflect the rates observed in clinical practice.

A phase 3 clinical trial evaluated the safety and efficacy of LAYOLIS Fe for pregnancy prevention. The study was a multicenter, non-comparative, open-label study with a treatment duration of 12 months (thirteen 28-day cycles). A total of 1,677 women aged 18-46 were enrolled and took at least one dose of LAYOLIS Fe.

Adverse Reactions Leading to Study Discontinuation: 8.5% of the women discontinued from the clinical trial due to an adverse reaction. The most common adverse reactions leading to discontinuation were nausea (1.0%), weight increase (0.8%), acne (0.8%), metrorrhagia (0.7%), altered mood (0.4%), hypertension (0.4%), irritability (0.3%), migraine (0.3%), decreased libido (0.3%) and mood swings (0.3%).

Common Adverse Reactions (≥ 2% of all treated subjects): nausea/vomiting (8.8%), headaches/migraine (7.5%), depression/mood complaints (4.1%), dysmenorrhea (3.9%), acne (3.2%), anxiety symptoms (2.4%), breast pain/tenderness (2.4%), and increased weight (2.3%).

Serious Adverse Reactions: Hypertension, depression, cholecystitis, and deep vein thrombosis.

6.2 Postmarketing Experience

Five studies that compared breast cancer risk between ever-users (current or past use) of COCs and never-users of COCs reported no association between ever use of COCs and breast cancer risk, with effect estimates ranging from 0.90 - 1.12 (Figure 1).

Three studies compared breast cancer risk between current or recent COC users (<6 months since last use) and never users of COCs (Figure 1). One of these studies reported no association between breast cancer risk and COC use. The other two studies found an increased relative risk of 1.19 - 1.33 with current or recent use. Both of these studies found an increased risk of breast cancer with current use of longer duration, with relative risks ranging from 1.03 with less than one year of COC use to approximately 1.4 with more than 8-10 years of COC use.

Figure 1.

RR = relative risk; OR = odds ratio; HR = hazard ratio. “ever COC” are females with current or past COC use; “never COC use” are females that never used COCs.

7 DRUG INTERACTIONS

No drug-drug interaction studies were conducted with LAYOLIS Fe.

7.1 Changes in Contraceptive Effectiveness Associated with Co-Administration of Other Products

If a woman on hormonal contraceptives takes a drug or herbal product that induces enzymes, including CYP3A4, that metabolize contraceptive hormones, counsel her to use additional contraception or a different method of contraception. Drugs or herbal products that induce such enzymes may decrease the plasma concentrations of contraceptive hormones, and may decrease the effectiveness of hormonal contraceptives or increase breakthrough bleeding. Some drugs or herbal products that may decrease the effectiveness of hormonal contraceptives include:

- barbiturates
- bosentan
- carbamazepine
- felbamate
- griseofulvin
- oxcarbazepine
- phenytoin
- rifampin
- St. John’s wort
- topiramate

HIV protease inhibitors and non-nucleoside reverse transcriptase inhibitors: Significant changes (increase or decrease) in the plasma levels of the estrogen and progestin have been noted in some cases of co-administration of HIV protease inhibitors or with non-nucleoside reverse transcriptase inhibitors.

Antibiotics: There have been reports of pregnancy while taking hormonal contraceptives and antibiotics, but clinical pharmacokinetic studies have not shown consistent effects of antibiotics on plasma concentrations of synthetic steroids.

Consult the labeling of all concurrently-used drugs to obtain further information about interactions with hormonal contraceptives or the potential for enzyme alterations.

7.2 Increase in Plasma Levels of Ethinyl Estradiol Associated with Co-Administered Drugs

Co-administration of atorvastatin and certain combination oral contraceptives containing ethinyl estradiol increase AUC values for ethinyl estradiol by approximately 20%. Ascorbic acid and acetaminophen may increase plasma ethinyl estradiol levels, possibly by inhibition of conjugation. CYP3A4 inhibitors such as itraconazole or ketoconazole may increase plasma hormone levels.

7.3 Concomitant Use with HCV Combination Therapy – Liver Enzyme Elevation

Do not co-administer LAYOLIS Fe with HCV drug combinations containing ombitasvir/paritaprevir/ritonavir, with or without dasabuvir, due to potential for ALT elevations [see Warnings and Precautions (5.4)].

7.4 Changes in Plasma Levels of Co-Administered Drugs

COCs containing some synthetic estrogens (e.g., ethinyl estradiol) may inhibit the metabolism of other compounds. COCs have been shown to significantly decrease plasma concentrations of lamotrigine, likely due to induction of lamotrigine glucuronidation. This may reduce seizure control; therefore, dosage adjustments of lamotrigine may be necessary. Consult the labeling of the concurrently-used drug to obtain further information about interactions with COCs or the potential for enzyme alterations.

8 USE IN SPECIFIC POPULATIONS

8.1 Pregnancy

Risk Summary

There is no use for contraception in pregnancy; therefore, LAYOLIS Fe should be discontinued during pregnancy. Epidemiologic studies and meta-analyses have not found an increased risk of genital or nongenital birth defects (including cardiac anomalies and limb-reduction defects) following exposure to COCs before conception or during early pregnancy.

In the U.S. general population, the estimated background risk of major birth defects and miscarriage in clinically recognized pregnancies is 2 to 4 percent and 15 to 20 percent, respectively.

8.2 Lactation

Risk Summary

Contraceptive hormones and/or metabolites are present in human milk. COCs can reduce milk production in breast-feeding females. This reduction can occur at any time but is less likely to occur once breast-feeding is well-established. When possible, advise the nursing female to use other methods of contraception until she discontinues breast-feeding [see Dosage and Administration (2.2)]. The developmental and health benefits of breast-feeding should be considered along with the mother’s clinical need for LAYOLIS Fe and any potential adverse effects on the breast-fed child from LAYOLIS Fe or from the underlying maternal condition.

8.4 Pediatric Use

Safety and efficacy of LAYOLIS Fe have been established in women of reproductive age. Efficacy is expected to be the same in postpubertal adolescents under the age of 18 years as for users 18 years and older. Use of this product before menarche is not indicated.

8.5 Geriatric Use

LAYOLIS Fe has not been studied in postmenopausal women and is not indicated in this population.

8.6 Renal Impairment

The pharmacokinetics of LAYOLIS Fe have not been studied in subjects with renal impairment.

8.7 Hepatic Impairment

No studies have been conducted to evaluate the effect of hepatic disease on the disposition of LAYOLIS Fe. However, steroid hormones may be poorly metabolized in patients with impaired liver function. Acute or chronic disturbances of liver function may necessitate the discontinuation of COC use until markers of liver function return to normal [see Contraindications (4), and Warnings and Precautions (5.3)].

8.8 Body Mass Index

The safety and efficacy of LAYOLIS Fe in women with a BMI > 35 kg/m^2 have not been evaluated.

10 OVERDOSAGE

There have been no reports of serious ill effects from overdose of oral contraceptives including ingestion by children. Overdosage may cause nausea, and withdrawal bleeding may occur in females.

11 DESCRIPTION

LAYOLIS Fe provides an oral contraceptive regimen consisting of 24 tablets that contain the active ingredients specified below, followed by four non-hormonal placebo tablets:

- 24 light green, round tablets each containing 0.8 mg norethindrone and 0.025 mg ethinyl estradiol
- 4 brown, round tablets each containing 75 mg ferrous fumarate

Each light green tablet also contains the following inactive ingredients: D&C Yellow No. 10 aluminum lake, FD&C Blue No. 1 aluminum lake, FD&C Yellow No. 6 aluminum lake, lactose monohydrate, magnesium stearate, mannitol, microcrystalline cellulose, povidone, sodium starch glycolate, spearmint flavor, sucralose and vitamin E.

Each brown, round tablet contains ferrous fumarate, magnesium stearate, mannitol, microcrystalline cellulose, povidone, sodium starch glycolate, spearmint flavor and sucralose. The ferrous fumarate chewable tablets do not serve any therapeutic purpose. Ferrous fumarate chewable tablets are not USP for dissolution and assay.

The empirical formula of ethinyl estradiol is C20H24O2 and the chemical structure is:

The chemical name of ethinyl estradiol is [19-Norpregna-1,3,5(10)-trien-20-yne-3,17-diol,(17α)-]

The empirical formula of norethindrone is C20H26O2 and the chemical structure is:

The chemical name of norethindrone is [17-hydroxy-19-nor-17α-pregn-4-en-20-yn-3-one]

12 CLINICAL PHARMACOLOGY

12.1 Mechanism of Action

CHCs lower the risk of becoming pregnant primarily by suppressing ovulation.

12.2 Pharmacodynamics

No specific pharmacodynamic studies were conducted with LAYOLIS Fe.

12.3 Pharmacokinetics

Absorption

Norethindrone and ethinyl estradiol are absorbed with maximum plasma concentrations occurring within 2 hours after LAYOLIS Fe administration (see Table 1). Both are subject to first-pass metabolism after oral dosing, resulting in an absolute bioavailability of approximately 64% for norethindrone and 43% for ethinyl estradiol.

The plasma norethindrone and ethinyl estradiol pharmacokinetics following single- and multiple-dose administrations of LAYOLIS Fe in 17 healthy female volunteers are provided in Table 1.

Following multiple-dose administration of LAYOLIS Fe, mean maximum concentrations of norethindrone and ethinyl estradiol were increased by 126% and 14%, respectively, as compared to single-dose administration. Mean norethindrone and ethinyl estradiol exposures (AUC values) were increased by 239% and 55% respectively, as compared to single-dose administration of LAYOLIS Fe.

Mean sex hormone binding globulin (SHBG) concentrations were increased by 170% from baseline (40.0 pg/mL; CV = 65%) to 108 pg/mL (CV = 45%) at steady-state.

Table 1. Pharmacokinetic Parameter Values Following Single and Multiple Dose Administration of LAYOLIS Fe
 | Arithmetic mean parameters (%CV)
Regimen | Analyte | Cmax | tmax | AUC 0 - 24h | t 1/2*
Day 1 (Single Dose) N = 17 | NE | 9,840 (36) | 1.4 (49) | 41,680 (47)
 | EE | 147 (25) | 1.2 (27) | 903 (18)
Day 24 (Multiple Dose) N = 17 | NE | 22,200 (30) | 1.6 (76) | 141,200 (32) | 10.8
 | EE | 168 (25) | 1.2 (35) | 1,400 (32) | 17.1

*The harmonic mean for t1/2 is presented

EE = ethinyl estradiol; NE = norethindrone
%CV = coefficient of variation; Cmax = maximum plasma concentration (pg/mL);
tmax = time of the maximum measured plasma concentration (h);
AUC0-24h = area under the plasma concentration versus time curve from time 0 to 24h (pg•h/mL); t1/2 = apparent elimination half life (h)

Food Effect

LAYOLIS Fe may be administered with or without food. A single-dose administration of LAYOLIS Fe with food decreased the maximum concentration of norethindrone by 47% and increased the extent of absorption by 10-14% and decreased the maximum concentration of ethinyl estradiol by 39% but not the extent of absorption.

Distribution

Volume of distribution of norethindrone and ethinyl estradiol ranges from 2 to 4 L/kg. Plasma protein binding of both steroids is extensive (> 95%); norethindrone binds to both albumin and SHBG, whereas ethinyl estradiol binds only to albumin. Although ethinyl estradiol does not bind to SHBG, it induces SHBG synthesis.

Metabolism

Norethindrone undergoes extensive biotransformation, primarily via reduction, followed by sulfate and glucuronide conjugation. The majority of metabolites in the circulation are sulfates, with glucuronides accounting for most of the urinary metabolites. A small amount of norethindrone is metabolically converted to ethinyl estradiol, such that exposure to ethinyl estradiol following administration of 1 mg of norethindrone acetate is equivalent to oral administration of 2.8 mcg ethinyl estradiol; therefore 0.8 mg norethindrone would be equivalent to the oral administration of 2.6 mcg ethinyl estradiol.

Ethinyl estradiol is also extensively metabolized, both by oxidation and by conjugation with sulfate and glucuronide. Sulfates are the major circulating conjugates of ethinyl estradiol and glucuronides predominate in urine. The primary oxidative metabolite is 2-hydroxy ethinyl estradiol, formed by the CYP3A4 isoform of cytochrome P450. Part of the first-pass metabolism of ethinyl estradiol is believed to occur in gastrointestinal mucosa. Ethinyl estradiol may undergo enterohepatic circulation.

Excretion

Norethindrone and ethinyl estradiol are excreted in both urine and feces, primarily as metabolites. Plasma clearance values for norethindrone and ethinyl estradiol are similar (approximately 0.4 L/hr/kg). Elimination half-lives of norethindrone and ethinyl estradiol following administration of 0.8 mg norethindrone / 0.025 mcg ethinyl estradiol tablets are approximately 11 hours and 17 hours, respectively.

Specific Populations

Pediatric Use: Safety and efficacy of LAYOLIS Fe have been established in women of reproductive age. Efficacy is expected to be the same for postpubertal adolescents under the age of 18 and for users 18 years and older. Use of this product before menarche is not indicated.

Geriatric Use: LAYOLIS Fe has not been studied in postmenopausal women and is not indicated in this population.

Renal Impairment: The pharmacokinetics of LAYOLIS Fe have not been studied in subjects with renal impairment.

Hepatic Impairment: The pharmacokinetics of LAYOLIS Fe have not been studied in subjects with hepatic impairment. Steroid hormones may be poorly metabolized in patients with impaired liver function. Acute or chronic disturbances of liver function may necessitate the discontinuation of COC use until markers of liver function return to normal [see Contraindications (4), and Warnings and Precautions (5.3)].

Body Mass Index: The efficacy of LAYOLIS Fe in women with a BMI of > 35 kg/m^2 has not been evaluated.

13 NONCLINICAL TOXICOLOGY

13.1 Carcinogenesis, Mutagenesis, Impairment of Fertility

[See Warnings and Precautions (5.2, 5.3)].

14 CLINICAL STUDIES

14.1 Oral Contraceptive Clinical Trial

In a one-year (thirteen 28-day cycles) multicenter, open-label clinical trial, 1,677 women 18 to 46 years of age were studied to assess the safety and efficacy of LAYOLIS Fe. The ethnic origin of the 1,570 treated subjects who were evaluable for efficacy was: Caucasian (72.0%), African-American (13.0%), Hispanic (11.2%) and Asian (1.8%). The weight range was 74 to 243 pounds with a mean weight of 148.8 pounds. Of treated women, 16.2% were lost to follow-up, 8.9% discontinued by withdrawing their consent and 8.5% discontinued due to an adverse event.

The pregnancy rate (Pearl Index) in 1,251 women 18 to 35 years of age was 2.01 (95% confidence interval 1.21, 3.14) pregnancies per 100 women-years of treatment based on 19 pregnancies that occurred after onset of treatment and within 7 days after the last pill in 12,297 cycles of treatment during which no back-up contraception was used.

16 HOW SUPPLIED/STORAGE AND HANDLING

16.1 How Supplied

LAYOLIS Fe® is available in cartons of 3 blister cards (dispensers) (NDC 52544-064-31).

Each blister card (28 tablets) contains in the following order:

- 24 light green, round tablets (active) imprinted with “WC” on one side and “483” on the other and each containing 0.8 mg norethindrone and 0.025 mg ethinyl estradiol.
- 4 brown, round tablets (non-hormonal placebo) imprinted with “WC” on one side and “624” on the other and each containing 75 mg ferrous fumarate.

16.2 Storage Conditions

Store at 20-25ºC (68-77ºF). [See USP controlled room temperature.]

Keep out of reach of children.

17 PATIENT COUNSELING INFORMATION

See FDA-Approved Patient Labeling

- Counsel patients that cigarette smoking increases the risk of serious cardiovascular events from COC use, and that women who are over 35 years old and smoke should not use COCs.
- Counsel patients that this product does not protect against HIV infection (AIDS) and other sexually transmitted diseases.
- Counsel patients on Warnings and Precautions associated with COCs.
- Counsel patients to chew one tablet daily by mouth without water at the same time every day in the exact order noted on the blister. Instruct patients what to do in the event pills are missed. See What Should I Do if I Miss any Pills section in FDA-Approved Patient Labeling [see Dosage and Administration (2.1)].
- Counsel patients to use a back-up or alternative method of contraception when enzyme inducers are used with LAYOLIS Fe.
- Counsel patients who are breastfeeding or who desire to breastfeed that COCs may reduce breast milk production. This is less likely to occur if breastfeeding is well established.
- Counsel any patient who starts COCs postpartum, and who has not yet had a period, to use an additional method of contraception until she has taken a light green tablet for 7 consecutive days.
- Counsel patients that amenorrhea may occur. Pregnancy should be ruled out in the event of amenorrhea in two or more consecutive cycles.

Distributed By:
Actavis Pharma, Inc.
Parsippany, NJ 07054

Revised: 3/2024

FDA-APPROVED PATIENT LABELING

Guide for Using LAYOLIS® Fe (norethindrone and ethinyl estradiol chewable tablets and ferrous fumarate chewable tablets)

WARNING TO WOMEN WHO SMOKE
Do not use LAYOLIS Fe if you smoke cigarettes and are over 35 years old. Smoking increases your risk of serious cardiovascular side effects (heart and blood vessel problems) from birth control pills, including death from heart attack, blood clots or stroke. This risk increases with age and the number of cigarettes you smoke.

Birth control pills help to lower the chances of becoming pregnant when taken as directed. They do not protect against HIV infection (AIDS) and other sexually transmitted diseases.

What is LAYOLIS Fe?

LAYOLIS Fe is a birth control pill. It contains two female hormones, an estrogen called ethinyl estradiol and a progestin called norethindrone.

How Do I Take LAYOLIS Fe?

- Chew and swallow one pill every day without water at the same time. Take the pills in the order directed on the blister pack.
- Do not skip pills or take at intervals exceeding 24 hours. If you miss pills (including starting the pack late), you could get pregnant. The more pills you miss, the more likely you are to get pregnant.
- If you have trouble remembering to take LAYOLIS Fe, talk to your healthcare provider about how to make pill‑taking easier or about using another method of birth control.
- You may have spotting or light bleeding when you first take LAYOLIS Fe. Spotting or light bleeding is normal at first.
- You may feel sick to your stomach (nauseated), especially during the first few months that you take LAYOLIS Fe. If you feel sick to your stomach, do not stop taking the pill. The problem will usually go away. If your nausea doesn't go away, call your healthcare provider.
- If you vomit or have diarrhea within 3-4 hours of taking your pill, follow the instructions for “What Should I Do if I Miss any Pills.”
- Missing pills can also cause spotting or light bleeding, even when you take the missed pills late. On the days you take 2 pills to make up for missed pills, you could also feel a little sick to your stomach.

How Well Does LAYOLIS Fe Work?

Your chance of getting pregnant depends on how well you follow the directions for taking your birth control pills. The more carefully you follow the directions, the less chance you have of getting pregnant.

Based on the results of one clinical study, 1 to 3 women out of 100 women may get pregnant during the first year they use LAYOLIS Fe.

The following chart shows the chance of getting pregnant for women who use different methods of birth control. Each box on the chart contains a list of birth control methods that are similar in effectiveness. The most effective methods are at the top of the chart. The box on the bottom of the chart shows the chance of getting pregnant for women who do not use birth control and are trying to get pregnant.

Before you start taking LAYOLIS Fe

- Decide what time of day to take your pill. It is important to take it at the same time every day and in the order as directed on the blister pack.

- Look at your LAYOLIS Fe blister pack. The blister pack has four rows of 7 pills each, for a total of 28 pills.
  Find:
  - where on the pack to start taking your pills
  - in what order to take the pills

Each LAYOLIS Fe blister pack has 28 pills

- 24 light green pills with hormones for Weeks 1, 2 and 3 and the first part of Week 4
- 4 brown pills without hormones for the remainder of Week 4

- Be sure to have ready at all times another kind of birth control (such as a condom and spermicide) to use as a back-up in case you miss pills.

When to Start LAYOLIS Fe

If you start taking LAYOLIS Fe and you did not use a hormonal birth control method before:

DAY-1 START:

- Pick the day label strip that starts with the first day of your period (this is the day you start bleeding or spotting, even if it is almost midnight when the bleeding begins). Pick a time of day that will be easy to remember.
- Place this day label strip on the tablet dispenser over the area that has the days of the week (starting with Sunday) printed on the plastic.
- Take the first light green pill of the first pack during the first 24 hours of your period.
- You will not need to use a back-up method of birth control because you are starting the pill at the beginning of your period. However, if you start on a day other than the first day of your period or if you are starting after having been pregnant and have not yet had a period, use a back-up method of birth control such as a condom and spermicide until you have taken a light green pill for 7 days in a row.
- After taking the last brown pill (day 28) of the blister pack, start taking the first light green pill from a new blister pack the very next day whether or not you are having your period.

If you start taking LAYOLIS Fe and you are switching from a combination hormonal method such as:

- another pill
- vaginal ring
- patch

- Take the first light green pill on the first day you would have started your previous birth control pack.
- If you previously used a vaginal ring or transdermal patch, finish the 21 days of use and wait 7 days after removal of the ring or transdermal patch before starting LAYOLIS Fe.
- Use a non-hormonal back-up method such as a condom and spermicide for the first 7 days you take LAYOLIS Fe.

If you start taking LAYOLIS Fe and you are switching from a progestin-only method such as a:

- progestin-only pill
- implant
- intrauterine system
- injection

- Take the first light green pill on the day you would have taken your next progestin-only pill or on the day of removal of your implant or intrauterine system or on the day when you would have had your next injection.
- Use a non-hormonal back-up method such as a condom and spermicide for the first 7 days you take LAYOLIS Fe.

What Should I do if I Miss any Pills

If you forgot to start a new blister pack, you may already be pregnant. Use back-up contraception (such as a condom and spermicide) anytime you have sex. Call your healthcare provider if you are unsure whether you are pregnant.

Your birth control pills may not be as effective if you miss any light green pills, and particularly if you miss the first few or the last few light green pills in a pack.

If you MISS ONE light green pill

- Take it as soon as you remember. Take the next pill at your regular time. This means you may take two pills in 1 day.
- You do not need to use a back‑up birth control method if you have sex.

If you MISS TWO light green pills in a row in WEEK 1 or WEEK 2 of your pack

- Take two pills on the day you remember and two pills the next day.
- Then take one pill a day until you finish the pack.
- You could become pregnant if you have sex during the 7 days after you restart your pills. You MUST use a non-hormonal birth control method (such as a condom and spermicide) as a back‑up for those 7 days.

If you MISS TWO light green pills in a row in WEEK 3 or WEEK 4 of your pack

- THROW OUT the rest of the pill pack and start a new pack that same day.
- You could become pregnant if you have sex during the 7 days after you restart your pills. You MUST use a non-hormonal birth control method (such as a condom and spermicide) as a back‑up for those 7 days after you restart your pills.

If you MISS THREE OR MORE light green pills in a row at any time

- THROW OUT the rest of the pill pack and start a new pack that same day.
- You could become pregnant if you have sex on the days when you missed pills or during the first 7 days after restarting your pills. You MUST use a non-hormonal birth control method (such as a condom and spermicide) as a back‑up the next time you have sex and for the first 7 days after you restart your pills.

If you forget any of the four brown "reminder" pills in WEEK 4

- THROW AWAY the pills you missed.
- Keep taking one pill each day until the pack is finished.
- You do not need to use a back‑up method of birth control.

You may already be pregnant or COULD BECOME PREGNANT if you had sex on the days after the pills were missed. The more pills missed and the closer they are to the end of the cycle, the higher the risk of a pregnancy. You should call your doctor or healthcare provider if you are unsure whether you are already pregnant.

If you are still not sure of what to do about the pills you have missed:

- Call your healthcare provider.
- Use a back-up contraception (such as a condom and spermicide) anytime you have sex and keep taking 1 pill each day.

Who Should not Take LAYOLIS Fe?

Your healthcare provider will not give you LAYOLIS Fe if you have:

- Ever had breast cancer, which may be sensitive to female hormones
- Liver disease, including liver tumors
- Take any Hepatitis C drug combination containing ombitasvir/paritaprevir/ritonavir, with or without dasabuvir. This may increase levels of the liver enzyme “alanine aminotransferase” (ALT) in the blood.
- Ever had blood clots in your arms, legs, or lungs
- Ever had a stroke
- Ever had a heart attack
- Certain heart valve problems or heart rhythm abnormalities that can cause blood clots to form in the heart
- An inherited problem with your blood that makes it clot more than normal
- High blood pressure that medicine can't control
- Diabetes with kidney, eye, or blood vessel damage
- Certain kinds of severe migraine headaches with aura, numbness, weakness or changes in vision

Also, do not take birth control pills if you:

- Smoke and are over 35 years old
- Are pregnant

Birth control pills may not be a good choice for you if you have ever had jaundice (yellowing of the skin or eyes) caused by pregnancy (also called cholestasis of pregnancy).

What Else Should I Know about Taking LAYOLIS Fe?

Birth control pills do not protect you against any sexually transmitted disease, including HIV, the virus that causes AIDS.

Do not skip any pills, even if you do not have sex often.

If you miss a period, you could be pregnant. However, some women miss periods or have light periods on birth control pills, even when they are not pregnant. Contact your healthcare provider for advice if you:

- Think you are pregnant
- Miss one period and have not taken your birth control pills according to directions
- Miss two periods in a row

Birth control pills should not be taken during pregnancy. However, birth control pills taken by accident during pregnancy are not known to cause birth defects.

You should stop LAYOLIS Fe at least four weeks before you have major surgery and not restart it until at least two weeks after the surgery due to an increased risk of blood clots.

If you are breastfeeding, consider another birth control method until you are ready to stop breastfeeding. Birth control pills that contain estrogen, like LAYOLIS Fe, may decrease the amount of milk you make. A small amount of the pill's hormones pass into breast milk.

Tell your healthcare provider about all medicines and herbal products that you take. Some medicines and herbal products may make birth control pills less effective, including:

- barbiturates
- bosentan
- carbamazepine
- felbamate
- griseofulvin
- oxcarbazepine
- phenytoin
- rifampin
- St. John’s wort
- topiramate

Consider using another birth control method when you take medicines that may make birth control pills less effective.

Birth control pills may interact with lamotrigine, an anticonvulsant used for epilepsy. This may increase the risk of seizures, so your healthcare provider may need to adjust the dose of lamotrigine.

If you have vomiting or diarrhea, your birth control pills may not work as well. Use another birth control method, like a condom and spermicide, until you check with your healthcare provider.

What are the Most Serious Risks of Taking Birth Control Pills?

Like pregnancy, birth control pills increase the risk of serious blood clots, especially in women who have other risk factors, such as smoking, obesity, or age greater than 35. It is possible to die from a problem caused by a blood clot, such as a heart attack or a stroke. Some examples of serious blood clots are blood clots in the:

- Legs (thrombophlebitis)
- Lungs (pulmonary embolus)
- Eyes (loss of eyesight)
- Heart (heart attack)
- Brain (stroke)

A few women who take birth control pills may get:

- High blood pressure
- Gallbladder problems
- Rare cancerous or noncancerous liver tumors

All of these events are uncommon in healthy women.

Call your healthcare provider right away if you have:

- Persistent leg pain
- Sudden shortness of breath
- Sudden blindness, partial or complete
- Severe pain in your chest
- Sudden, severe headache unlike your usual headaches
- Weakness or numbness in an arm or leg, or trouble speaking
- Yellowing of the skin or eyeballs

What are the Common Side Effects of Birth Control Pills?

The most common side effects of birth control pills are:

- Spotting or bleeding between menstrual periods
- Nausea
- Breast tenderness
- Headache

These side effects are usually mild and usually disappear with time.

Less common side effects are:

- Acne
- Less sexual desire
- Bloating or fluid retention
- Blotchy darkening of the skin, especially on the face
- High blood sugar, especially in women who already have diabetes
- High fat levels in the blood
- Depression, especially if you have had depression in the past. Call your healthcare provider immediately if you have any thoughts of harming yourself.
- Problems tolerating contact lenses
- Weight changes

This is not a complete list of possible side effects. Talk to your healthcare provider if you develop any side effects that concern you. You may report side effects to the FDA at 1-800-FDA-1088.

No serious problems have been reported from a birth control pill overdose, even when accidentally taken by children.

Do Birth Control Pills Cause Cancer?

It is not known if hormonal birth control pills cause breast cancer. Some studies, but not all, suggest that there could be a slight increase in the risk of breast cancer among current users with longer duration of use.

If you have breast cancer now, or have had it in the past, do not use hormonal birth control because some breast cancers are sensitive to hormones.

Women who use birth control pills may have a slightly higher chance of getting cervical cancer. However, this may be due to other reasons such as having more sexual partners.

What Should I Know about My Period when Taking LAYOLIS Fe?

Unscheduled (irregular) vaginal bleeding or spotting may occur while you are taking LAYOLIS Fe. Unscheduled bleeding may vary from slight staining to breakthrough bleeding, which is a flow much like a regular period, but which occurs between menstrual periods. Unscheduled bleeding occurs most often during the first few months of oral contraceptive use, but may also occur after you have been taking the pill for some time. Such bleeding may be temporary and usually does not indicate any serious problems.

Approximately one-third of the women who use LAYOLIS Fe have unscheduled bleeding or spotting in the first months of use. About one-quarter of users continue to have unscheduled bleeding or spotting after one year of use.

It is important to continue taking your pills on schedule. If the bleeding occurs in more than one cycle, is unusually heavy, or lasts for more than a few days, call your healthcare provider.

What if I Miss My Scheduled Period when Taking LAYOLIS Fe?

Women who use LAYOLIS Fe may not have a period at the end of every 28-day pack of pills.

If you miss more than two periods in a row or miss one period when you have not taken your birth control pills according to directions, call your healthcare provider. Also notify your healthcare provider if you have symptoms of pregnancy such as morning sickness or unusual breast tenderness. It is important that your healthcare provider checks you to find out if you are pregnant. Stop taking LAYOLIS Fe if you are pregnant.

What If I Want to Become Pregnant?

You may stop taking the pill whenever you wish. Consider a visit with your healthcare provider for a pre-pregnancy checkup before you stop taking the pill.

General Advice about LAYOLIS Fe

Your healthcare provider prescribed LAYOLIS Fe for you. Please do not share LAYOLIS Fe with anyone else. Keep LAYOLIS Fe out of the reach of children.

If you have concerns or questions, ask your healthcare provider. You may also ask your healthcare provider for a more detailed label written for medical professionals.

For more information contact Actavis Medical Communications at 1-888-838-2872.

For all medical inquiries contact:
ACTAVIS
Medical Communications
Parsippany, NJ 07054 USA
1-888-838-2872

Distributed By:
Actavis Pharma, Inc.
Parsippany, NJ 07054

Revised: 3/2024

PRINCIPAL DISPLAY PANEL

NDC 52544-064-31
Layolis™ Fe
(norethindrone and ethinyl estradiol chewable tablets
and ferrous fumarate chewable tablets) 0.8 mg/25 mcg
Three 28-Tablet Dispensers
Rx Only